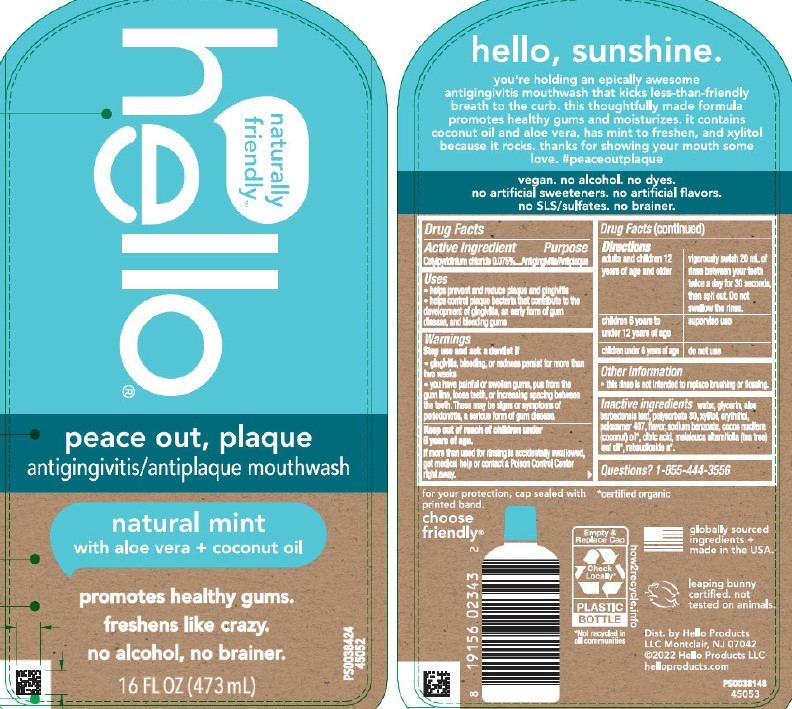 DRUG LABEL: Hello Peace Out Plaque
NDC: 44038-0683 | Form: MOUTHWASH
Manufacturer: Accupac LLC
Category: otc | Type: HUMAN OTC DRUG LABEL
Date: 20260122

ACTIVE INGREDIENTS: CETYLPYRIDINIUM CHLORIDE 15 mg/20 mL
INACTIVE INGREDIENTS: ALOE VERA LEAF; ERYTHRITOL; COCONUT OIL; SODIUM BENZOATE; STEVIA REBAUDIUNA LEAF; POLYSORBATE 80; TEA TREE OIL; WATER; ANHYDROUS CITRIC ACID; XYLITOL; POLOXAMER 407; GLYCERIN

Hello Peace Out Plaque

peace out, plaque antigingivitis

Active ingredient

Cetylpyridinium chloride 0.075%

Purpose

Antigingivitis/Antiplaque

Use

helps prevent and reduce plaque and gingivitis

helps control plaque bacteria that contribute to the development of gingivitis, an early form of gum disease, and bleeding gums

WARNINGS

Stop use and ask a dentist if

gingivitis, bleeding, or redness persist for more than two weeks

you have painful or swollen gums, pus from the gum line, loose teeth, or increasing space between the teeth.These may be signs or symptoms of periodontitis, a serious form of gum disease.

Keep out of the reach of children under 6 years of age.

If more than used for rinsing is accidentally swallowed, get medical help or contact a Poison Control Center right away.

Directions

adults and children 12 years of age and older-vigorously swish 20mL of rinse between your teeth twice day for 30 seconds, then spit out. Do not swallow the rinse.

children 6 years to under 12 years of age-supervise use

children under 6 years of age-do not use

Other information

This rinse is not intended to replace brushing or flossing.

Inactive ingredients

water, glycerin, aloe barbadensis leaf, polysorbate 80, xylitol, erythritol, poloxamer 407, flavor, sodium benzoate, cocos nucifera (coconut) oil 1, citric acid, melaleuca alternifolia (tea tree) leaf oil 1, rabaudioside a 1.

1 certified organic

Questions?

1-855-444-3556

Dist. by Hello Products

LLC Montclair, NJ 07042

Principal Display Panel-473 mL Bottle label

naturally

friendly

hello

peace out, plaque

antigingivitis/antiplaque mouthwash

natural mint

with aloe vera + coconut oil

promotes healthy gums.

freshens like crazy.

no alcohol, no brainer.

16 FL. OZ. (473 mL)

PS0038424

45052